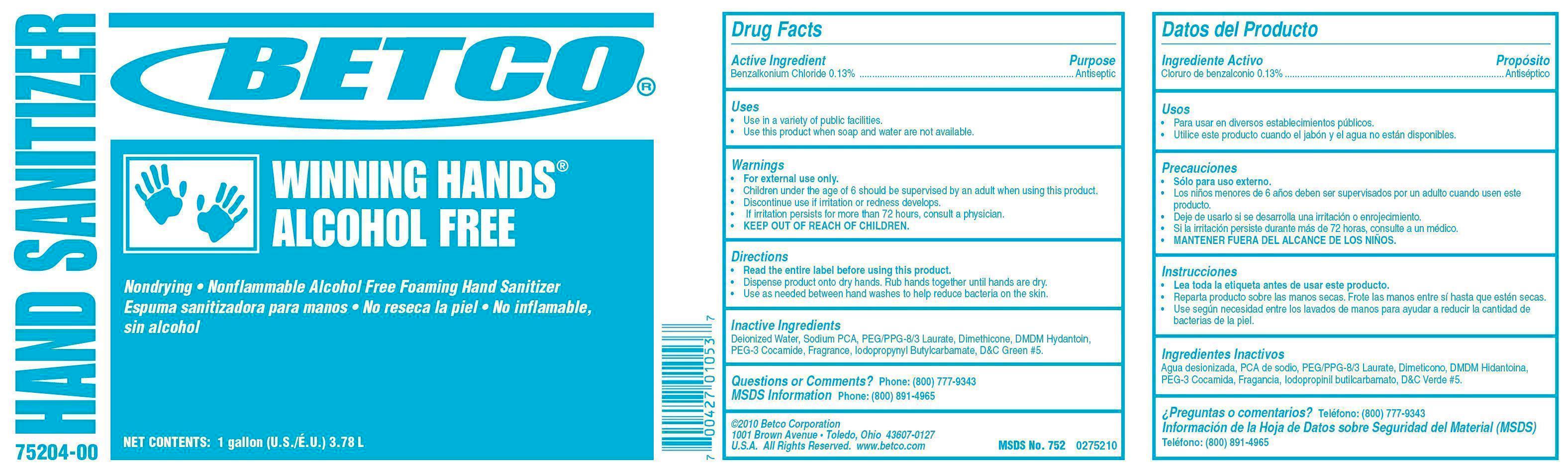 DRUG LABEL: Winning Hands Alcohol Free
NDC: 65601-752 | Form: SOAP
Manufacturer: Betco Corporation, Ltd.
Category: otc | Type: HUMAN OTC DRUG LABEL
Date: 20160919

ACTIVE INGREDIENTS: BENZALKONIUM CHLORIDE 1.3 mg/1 mL
INACTIVE INGREDIENTS: WATER; SODIUM PYRROLIDONE CARBOXYLATE; POLYETHYLENE GLYCOL 400; DIMETHICONE; DMDM HYDANTOIN; PEG-6 COCAMIDE; IODOPROPYNYL BUTYLCARBAMATE; D&C GREEN NO. 5

Winning Hands Alcohol Free

Winning Hands Alcohol Free

Active Ingredient

Benzalkonium Chloride 0.13%

Winning Hands Alcohol Free

Uses

- Use in a variety of public facilities.
- Use this product when soap and water are not available.

Winning Hands Alcohol Free

Warnings

- For external use only.
- Avoid contact with eyes.
- Children under the age of 6 should be supervised by an adult when using this product.
- Discontinue use is irritation or redness develops.
- If irritation persists for more than 72 hours, consult a physician.
- KEEP OUT OF REACH OF CHILDREN.

Winning Hands Alcohol Free

Directions

- Read the entire label before using this product.
- Dispense product onto dry hands. Rub hands together until hands are dry.
- Use as needed between hand washes to reduce bacteria on the skin.

Winning Hands Alcohol Free

Inactive Ingredients

Deionized Water, Sodium PCA, PEG/PPG-8/3 Laurate, Dimethicone, DMDM Hydantoin, PEG-3 Cocamide, Fragrance, Iodoproynyl Btylcarbamate, D&C Green #5.

Winning Hands Alcohol Free

Questions or Comments? Phone: (800) 777-9343

MDS information:(800) 891-4965

Winning Hands Alcohol Free

Purpose

Antiseptic

Winning Hands Alcohol Free

KEEP OUT OF REACH OF CHILDREN

Winning Hands Alcohol Free

Nondrying-Nonflammable Alcohol Free Foaming Hand Sanitizer

Net Contents: 1 gallon (U.S./E.U.) 3.78 L